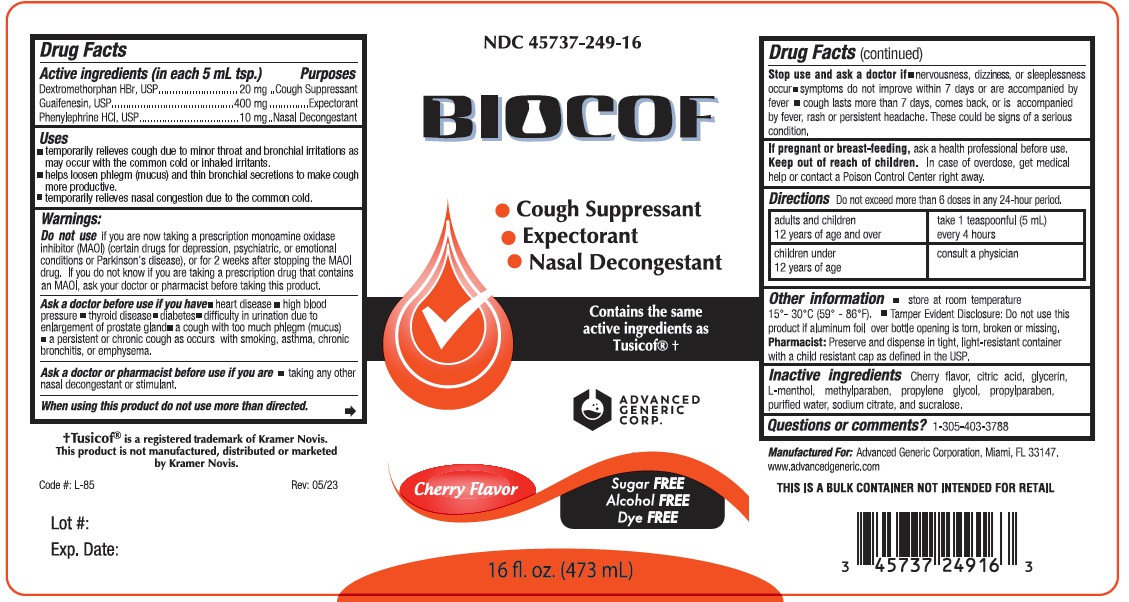 DRUG LABEL: Biocof
NDC: 45737-249 | Form: LIQUID
Manufacturer: Advanced Generic Corporation
Category: otc | Type: HUMAN OTC DRUG LABEL
Date: 20251230

ACTIVE INGREDIENTS: DEXTROMETHORPHAN HYDROBROMIDE 20 mg/5 mL; GUAIFENESIN 400 mg/5 mL; PHENYLEPHRINE HYDROCHLORIDE 10 mg/5 mL
INACTIVE INGREDIENTS: CITRIC ACID MONOHYDRATE; GLYCERIN; MENTHOL; METHYLPARABEN; SODIUM CITRATE; PROPYLENE GLYCOL; SUCRALOSE; WATER; PROPYLPARABEN

AGC-Biocof 249

Active Ingredients (in each 5 mL tps.) Purpose

Dextromethorphan Hydrobromide.... 20 mg...........................Cough suppressant

Guaifenesin.... 400 mg........................................................Expectorant

Phenylephrine HCL.....10 mg...............................................Nasal Decogestant

Uses:

- temporary relieves cough due to minor throat and bronchial irritations as may occur with the common cold or inhaled irritants.
- Helps loosen phlegm (mucus) and thin bronchial secretions to make cough more productive temporarily relieves nasal congestion due to the common cold

Warnings:

Ask a doctor before use if you have:

- Heart disease
- high blood pressure
- thyroid disease
- diabetes
- difficulty in urination due to an enlarged prostate gland
- a cough with too much phlegm (mucus)
- a persistent or chronic cough as occurs with smoking, asthma, chronic bronchitis, or emphysema.

Ask a doctor before use if you have

- heart disease
- high blood pressure
- thyroid disease
- diabetes
- difficulty in urination due to enlargment or prostate gland
- a cough with too much phlegm (mucus)
- a persistent or chronic cough as occurs with smoking asthma, chronic bronchitis, or emphysema

Ask a doctor or pharmacist before useif you are taking any other nasal decongestant or stimulant.

When using this product do not use more than directed.

Stop use and ask a doctor if:you get nervous, dizzy, or sleepless; symptoms do not get better within 7 days, or are accompanied by fever

- cough lasts more than 7 days, comes back, or is accompanied by a fever, rash or persistent headache. These could be signs of serious condition.

Do not use:

If you are now taking a prescription monoamine oxidase inhibitor (MAOI) (certain drugs of depression, psychiatric, or emotional conditions or Parkinson's disease), or for 2 weeks after stopping the MAOI drug. If you do not know if you are taking a prescription drug that contains MAOI; ask your doctor or pharmacist before taking this product.

KEEP OUT OF REACH OF CHILDREN

Keep out of the reach of children.In case of overdose, get medical help or contact a Poison Control Center right away.

PREGNANCY OR BREAST FEEDING

If pregnant or breast-feeding,ask a health professional before use.

DOSAGE AND ADMINISTRATION

DirectionsDo not exceed more than 6 doses in any 24 hours period.

Adults and children 12 years of age and over. | Take 1 teaspoonful (5 mL) every 4 hours
Children under 12 years of age. | Consult a physician

Uses

- temporary relives cough due to minor throat and bronchial irritations as may occur with the common cold or inhaled irritants
- helps loosen phlegm (mucus) and thin bronchial secretions to make cough more productive temporarily relieves nasal congestion due to the common cold

INACTIVE INGREDIENT

Inactive Ingredients:Cherry flavor, Citric Acid, Glycerin, menthol, methylparaben, propylene glycol, propylparaben, purified water, sodium citrate, sucralose, sucralose

Questions or comments? 1-305-403-3788
Manufactured for:Advanced Generic Corporation
Miami, FL 33166